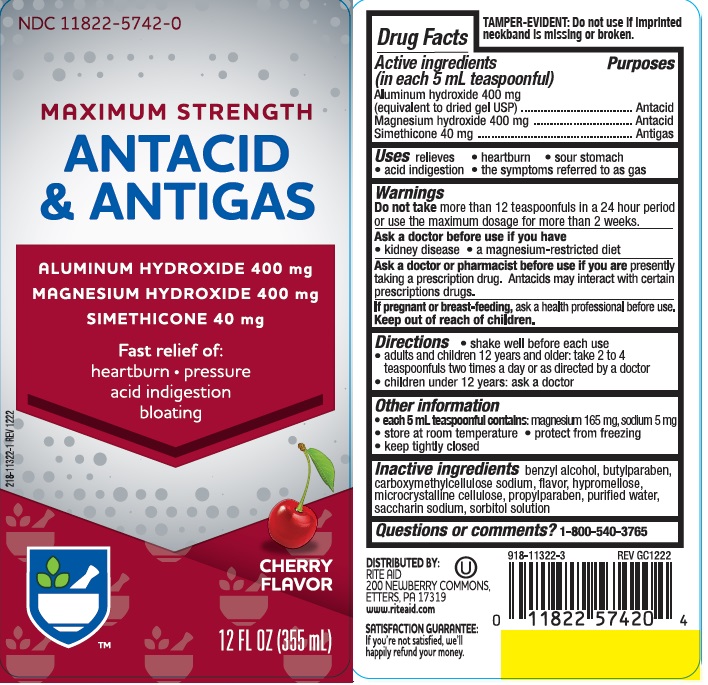 DRUG LABEL: MAXIMUM STRENGTH ANTACID AND ANTIGAS
NDC: 11822-5742 | Form: LIQUID
Manufacturer: RITE AID PHARMACY
Category: otc | Type: HUMAN OTC DRUG LABEL
Date: 20251119

ACTIVE INGREDIENTS: ALUMINUM HYDROXIDE 400 mg/5 mL; MAGNESIUM HYDROXIDE 400 mg/5 mL; DIMETHICONE 40 mg/5 mL
INACTIVE INGREDIENTS: BENZYL ALCOHOL; BUTYLPARABEN; CARBOXYMETHYLCELLULOSE SODIUM; HYPROMELLOSES; CELLULOSE, MICROCRYSTALLINE; PROPYLPARABEN; WATER; SACCHARIN SODIUM; SORBITOL SOLUTION

riteaid antacid max cherry

Active ingredients (in each 5 mL teaspoonful)

Aluminum hydroxide 400mg (equivalent to dried gel, USP)
Magnesium hydroxide 400 mg
Simethicone 40mg

Purposes

Antacid

Antigas

Uses

relieves

- heartburn
- sour stomach
- acid indigestion
- the symptoms referred to as gas

Warnings

Do not take more than 12 teaspoonfuls in a 24 hour period or use the maximum dosage for more than 2 weeks

Ask a doctor before use if you have

- kidney disease
- a magnesium-restricted diet

Ask a doctor or pharmacist before use if you are

taking a prescription drug.
Antacids may interact with certain prescription drugs.

If pregnant or breast-feeding,

ask a health professional before use.

Keep out of reach of children.

Directions

- shake well before each use
- adults and children 12 years of age and older: take 2 to 4 teaspoonfuls two times a day or as directed by a doctor
- children under 12 years: ask a doctor

Other information

- each 5 mL teaspoonful contains: magnesium 165 mg, sodium 5 mg
- do not freeze
- store at room temperature tightly closed

Inactive ingredients

benzyl alcohol, butylparaben, carboxymethylcellulose sodium, flavor, hypromellose, microcrystalline cellulose, propylparaben, purified water, saccharin sodium, sorbitol solution

Questions or comments?

1-800-540-3765